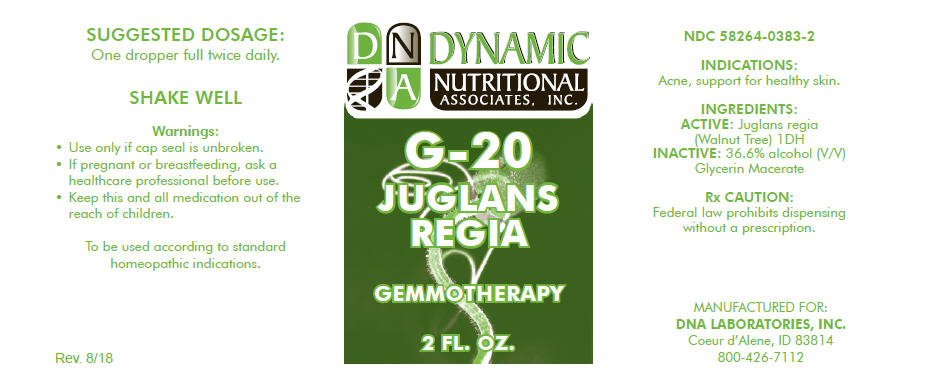 DRUG LABEL: G-20
NDC: 58264-0383 | Form: SOLUTION
Manufacturer: DNA Labs, Inc.
Category: homeopathic | Type: HUMAN OTC DRUG LABEL
Date: 20250109

ACTIVE INGREDIENTS: JUGLANS REGIA FLOWERING TOP 1 [hp_X]/1 mL
INACTIVE INGREDIENTS: ALCOHOL; WATER

G-20

NDC 58264-0383-2

INDICATIONS

PURPOSE

Acne, support for healthy skin.

INGREDIENTS

ACTIVE

Juglans regia (Walnut Tree) 1DH

INACTIVE

36.6% alcohol (V/V) Glycerin Macerate

Rx CAUTION

Federal law prohibits dispensing without a prescription.

SUGGESTED DOSAGE

One dropper full twice daily.

STORAGE AND HANDLING

SHAKE WELL

Warnings

- Use only if cap seal is unbroken.

PREGNANCY OR BREAST FEEDING

- If pregnant or breastfeeding, ask a healthcare professional before use.

KEEP OUT OF REACH OF CHILDREN

- Keep this and all medication out of the reach of children.

To be used according to standard homeopathic indications.

PRINCIPAL DISPLAY PANEL - 2 FL. OZ. Bottle Label

DYNAMIC
NUTRITIONAL
ASSOCIATES, INC.

G-20

JUGLANS
REGIA

GEMMOTHERAPY

2 FL. OZ.